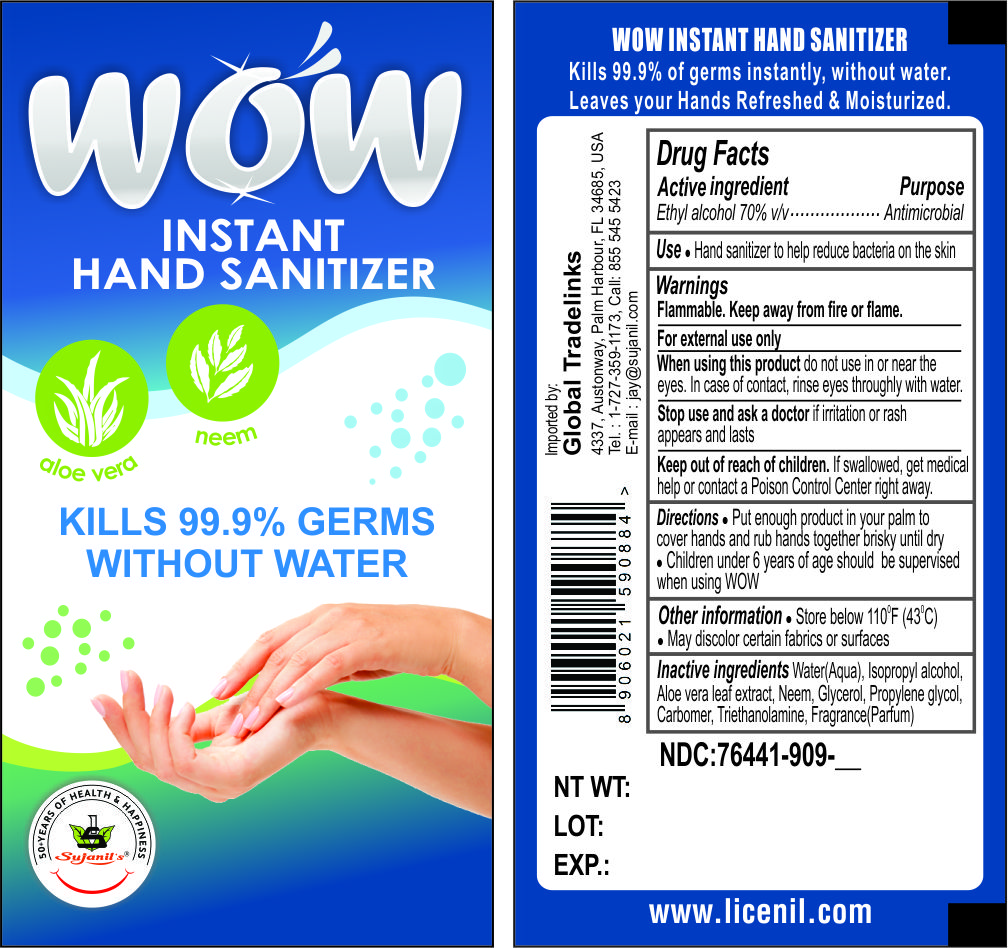 DRUG LABEL: Sujanils WOW Instant Hand Sanitiser
NDC: 76441-999 | Form: GEL
Manufacturer: Sujanil Chemo Industries
Category: otc | Type: HUMAN OTC DRUG LABEL
Date: 20200812

ACTIVE INGREDIENTS: ALCOHOL 70 mL/100 mL
INACTIVE INGREDIENTS: WATER; ALOE VERA LEAF; ISOPROPYL ALCOHOL; GLYCERIN; AZADIRACHTA INDICA SEED OIL; CARBOMER INTERPOLYMER TYPE A (55000 CPS); PROPYLENE GLYCOL

Sujanil's WOW Instant Hand Sanitiser

Sujanil's WOW Instant Hand Sanitiser

WOW Instant Hand Sanitiser Kills 99.9% germs Instantly

a. Alcohol (Ethanol) (70%, volume/volume(v/v).

b. Glycerol (0.5% v/v).

c. Aloe vera (0.5% v/v)

d. Sterile distilled water or Boiled cold water.

Active Ingredients

Ethyl Alcohol 70% v/v. Purpose: Antiseptic, Antimicrobial, Hand Sanitizer

Purpose

Antiseptic, Antimicrobial, Hand Sanitiser

Use

WOW Instant Hand Sanitiser to help reduce bacteria that potentially can cause disease. For use soap and water are not available

Warnings

For External Use Only. Flammable. Keep away from heat or flame

Do not use

- in Children less than 2 months of age
- on open skin wounds

When using this product keep out of eyes, ears, and mouth. In case of contact with eyes, rinse eyes thoroughly with water.

Stop use and ask a doctor if irritation or rash occurs. These may be signs of a serious condition.

Keep out of reach of children. If swallowed, get medical help or contact a Poison Control Center right away.

Stop use and ask a doctor if irritation or rash occurs. These may be signs of a serious condition.

Keep out of reach of children. If swallowed, get medical help or contact a Poison Control Center right away.

Directions

- Place enough product on hands to cover all surfaces. Rub hands together until dry.
- Supervise children under 6 years of age when using this product to avoid swallowing.

Other information

- Store between 15-30C (59-86F)
- Avoid freezing and excessive heat above 40C (104F)

Inactive ingredients

Water(Aqua), Isopropyl Alcohol, Aloe vera leaf extract, Neem, Glycerol, Propylene glycol, Carbomer, Triethanolamine, Fragrance(Parfum)

Package Label - Principal Display Panel

000 mL NDC: 76441-909-__